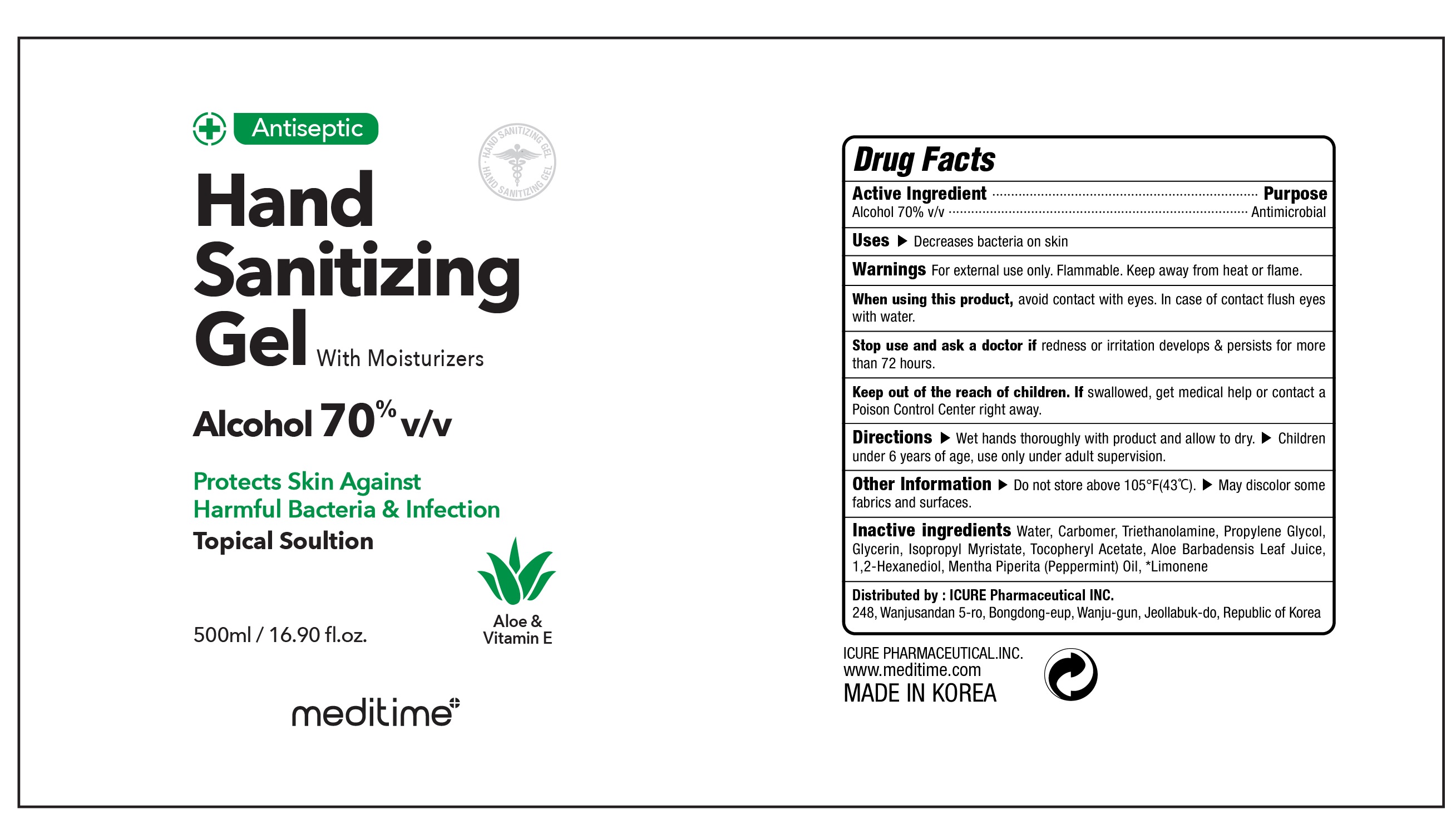 DRUG LABEL: Meditime Hand Sanitizing
NDC: 73279-0002 | Form: GEL
Manufacturer: Icure Pharmaceutical Inc, Wanju Factory
Category: otc | Type: HUMAN OTC DRUG LABEL
Date: 20200426

ACTIVE INGREDIENTS: ALCOHOL 350 mL/500 mL
INACTIVE INGREDIENTS: Water; CARBOMER HOMOPOLYMER, UNSPECIFIED TYPE; TROLAMINE; Propylene Glycol; Glycerin; Isopropyl Myristate; .ALPHA.-TOCOPHEROL ACETATE; ALOE VERA LEAF; 1,2-Hexanediol; PEPPERMINT OIL; LIMONENE, (+)-

Active Ingredients

Active ingredients: Alcohol 70% v/v

INACTIVE INGREDIENT

Inactive ingredients:

Water, Carbomer, Triethanolamine, Propylene Glycol, Glycerine, Isopropyl Myristate, Tocopheryl Acetate, Aloe Barbadensis Leaf Juice, 1,2-Hexanediol, Mentha Piperita (Peppermint) Oil, Limonene

Purpose

Purpose: Antimicrobial

Warnings

For external use only. Flammable.
Keep away from heat or flame.
--------------------------------------------------------------------------------------------------------
When using this product, avoid contact with eyes. In case of contact flush eyes with water.
--------------------------------------------------------------------------------------------------------
Stop use and ask a doctor if redness or irritation develops & persists for more than 72 hours.

Keep out of reach of children. If swallowed, get medical help or contact a Poison Control Center right away.

Uses

Decrease bacteria on hands

Directions

Wet hands thoroughly with product and allow to dry.
Children under 6 years of age, use only under adult supervision.

Other information

Do not store above 105℉(43℃)
May discolor some fabrics and surfaces